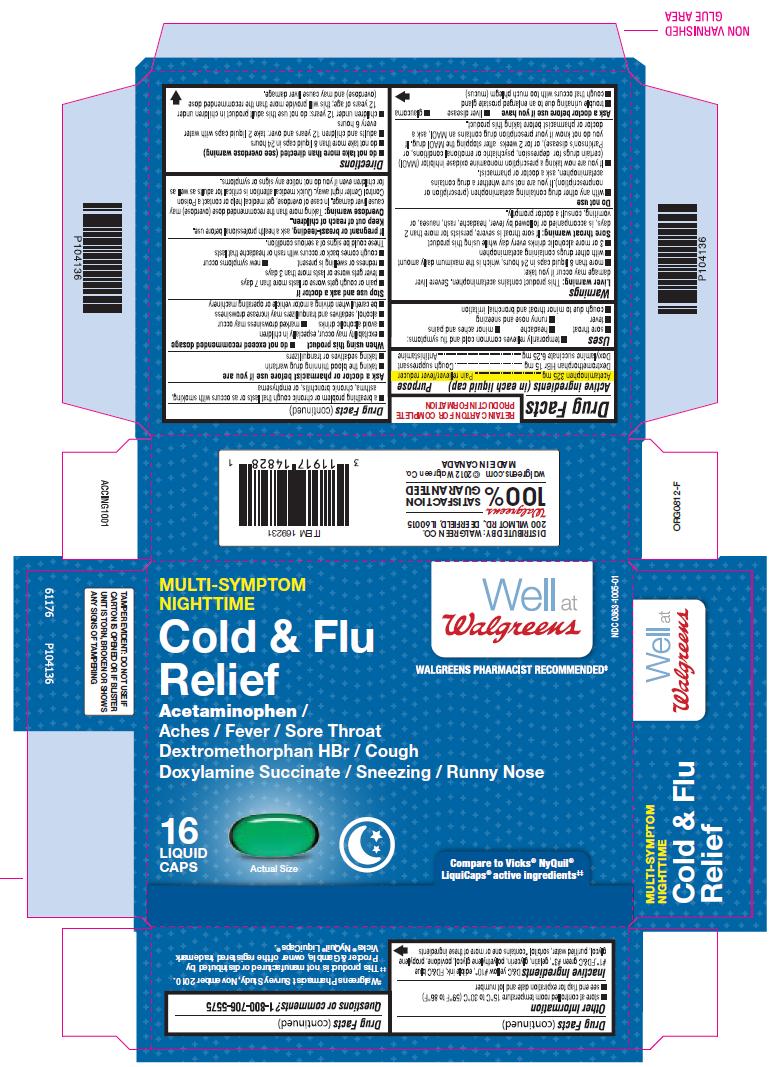 DRUG LABEL: nighttime cold and flu relief
NDC: 0363-1005 | Form: CAPSULE, LIQUID FILLED
Manufacturer: Walgreen Company
Category: otc | Type: HUMAN OTC DRUG LABEL
Date: 20121004

ACTIVE INGREDIENTS: ACETAMINOPHEN 325 mg/1 1; DEXTROMETHORPHAN HYDROBROMIDE 15 mg/1 1; DOXYLAMINE SUCCINATE 6.25 mg/1 1
INACTIVE INGREDIENTS: D&C YELLOW NO. 10; FD&C BLUE NO. 1; FD&C GREEN NO. 3; GELATIN; GLYCERIN; POLYETHYLENE GLYCOLS; POVIDONES; PROPYLENE GLYCOL; WATER; SORBITOL

Walgreen Co. Nighttime Cold & Flu Relief Drug Facts

Active ingredients (in each liquid cap)

Acetaminophen 325 mg

Dextromethorphan HBr 15 mg

Doxylamine succinate 6.25 mg

Purpose

Pain reliever/fever reducer

Cough suppressant

Antihistamine

Uses

temporarily relieves common cold and flu symptoms:

- sore throat
- headache
- minor aches and pains
- fever
- runny nose and sneezing
- cough due to minor throat and broncial irritation

Warnings

Liver warning: This product contains acetaminophen. Severe liver damage may occur if you take:

- more than 8 liquid caps in 24 hours, which is the maximum daily amount
- with other drugs containing acetaminophen
- 3 or more alcoholic drinks every day while using this product

Sore throat warning:If sore throat is severe, persists for more than 2 days, is accompanied or followed by fever, headache, rash, nausea, or vomiting, consult a doctor promptly.

Do not use

- with any other drug containing acetaminophen (prescription or nonprescription). If you are not sure whether a drug contains acetaminophen, ask a doctor or pharmacist.
- If you are now taking a prescription monoamine oxidase inhibitor (MAOI) (certain drugs for depression, psychiatric or emotional conditions, or Parkinson’s disease), or for 2 weeks after stopping the MAOI drug. If you do not know if your prescription drug contains an MAOI, ask a doctor or pharmacist before taking this product.

Ask a doctor before use if you have

- liver disease
- glaucoma
- trouble urinating due to an enlarged prostate gland
- cough that occurs with too much phlegm (mucus)
- a breathing problem or chronic cough that lasts or as occurs with smoking, asthma, chronic bronchitis, or emphysema

Ask a doctor or pharmacist before use if you are

- taking the blood thinning drug warfarin
- taking sedatives or tranquilizers

When using this product

- do not exceed recommended dosage
- excitability may occur, especially in children
- avoid alcoholic drinks
- marked drowsiness may occur
- alcohol, sedatives and tranquilizers may increase drowsiness
- be careful when driving a motor vehicle or operating machinery

Stop use and ask a doctor if

- pain or cough gets worse or lasts more than 7 days
- fever gets worse or lasts more than 3 days
- redness or swelling is present
- new symptoms occur
- cough comes back or occurs with rash or headache that lasts

These could be signs of a serious condition.

If pregnant or breast-feeding,

ask a health professional before use.

Keep out of reach of children.

Overdose warning: Taking more than the recommended dose (overdose) may cause liver damage. In case of overdose, get medical help or contact a Poison Control Center right away. Quick medical attention is critical for adults as well as for children even if you do not notice any signs or symptoms.

Directions

- do not take more than directed (see overdose warning)
- do not take more than 8 liquid caps in 24 hours
- adults and children 12 years and over: take 2 liquid caps with water every 6 hours
- children under 12 years: do not use this adult product in children under 12 years of age; this will provide more than the recommended dose (overdose) and may cause liver damage.

Other information

- store at controlled room temperature 15°C to 30°C (59°F to 86°F)
- see end flap for expiration date and lot number

Inactive ingredients

D&C yellow #10*, edible ink, FD&C blue #1*, FD&C green #3*, gelatin, glycerin, polyethylene glycol, povidone, propylene glycol, purified water, sorbitol, * contains one or more of these ingredients

Questions or comments?

1-800-706-5575

Principal Display Panel

MULTI-SYMPTOM NIGHTTIME

Cold & Flu Relief

Acetaminophen / Aches / Fever / Sore throat

Dextromethorphan HBr / Cough

Doxylamine Succinate / Sneezing / Runny Nose

Compare to Vicks® NyQuil® active ingredients‡